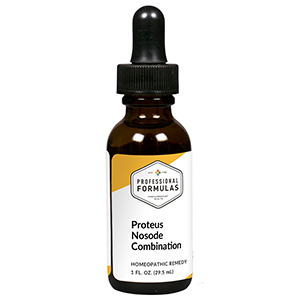 DRUG LABEL: Proteus Nosode Combination
NDC: 63083-9415 | Form: LIQUID
Manufacturer: Professional Complementary Health Formulas
Category: homeopathic | Type: HUMAN OTC DRUG LABEL
Date: 20190815

ACTIVE INGREDIENTS: GELSEMIUM SEMPERVIRENS ROOT 3 [hp_X]/29.5 mL; COLCHICUM AUTUMNALE BULB 4 [hp_X]/29.5 mL; CITRULLUS COLOCYNTHIS FRUIT PULP 6 [hp_X]/29.5 mL; STRYCHNOS NUX-VOMICA SEED 6 [hp_X]/29.5 mL; PROTEUS INCONSTANS 12 [hp_X]/29.5 mL; MERCURIC CHLORIDE 12 [hp_X]/29.5 mL
INACTIVE INGREDIENTS: ALCOHOL; WATER

R415

ACTIVE INGREDIENTS

Gelsemium sempervirens 3X
Colchicum autumnale 4X
Colocynthis 6X
Nux vomica 6X
Bacillus proteus 12X
Mercurius corrosivus 12X

QUESTIONS

Professional Formulas

PO Box 2034 Lake Oswego, OR 97035

INDICATIONS

For the temporary relief of urinary discomfort, difficulty or increased frequency, minor back pain, fatigue, nausea, vomiting, or diarrhea.*

PURPOSE

*Claims based on traditional homeopathic practice, not accepted medical evidence. Not FDA evaluated.

WARNINGS

Persistent symptoms may be a sign of a serious condition. If symptoms persist or are accompanied by a fever, rash, blood in urine, or persistent headache, consult a doctor. Keep out of the reach of children. In case of overdose, get medical help or contact a poison control center right away. If pregnant or breastfeeding, ask a healthcare professional before use.

Keep out of the reach of children.

PREGNANCY OR BREAST FEEDING

If pregnant or breastfeeding, ask a healthcare professional before use.

DIRECTIONS

Place drops under tongue 30 minutes before/after meals. Adults and children 12 years and over: Take 10 to 15 drops once weekly or monthly. If mild symptoms are present, take 10 drops up to 3 times per day. Consult a physician for use in children under 12 years of age.

OTHER INFORMATION

Tamper resistant. If seal is broken, do not use. After opening, close container tightly and store at room temperature away from heat.

INACTIVE INGREDIENTS

40% ethanol, purified water.

LABEL

Est 1985

Professional Formulas

Complementary Health

Proteus Nosode Combination

Homeopathic Remedy

1 FL. OZ. (29.5 mL)